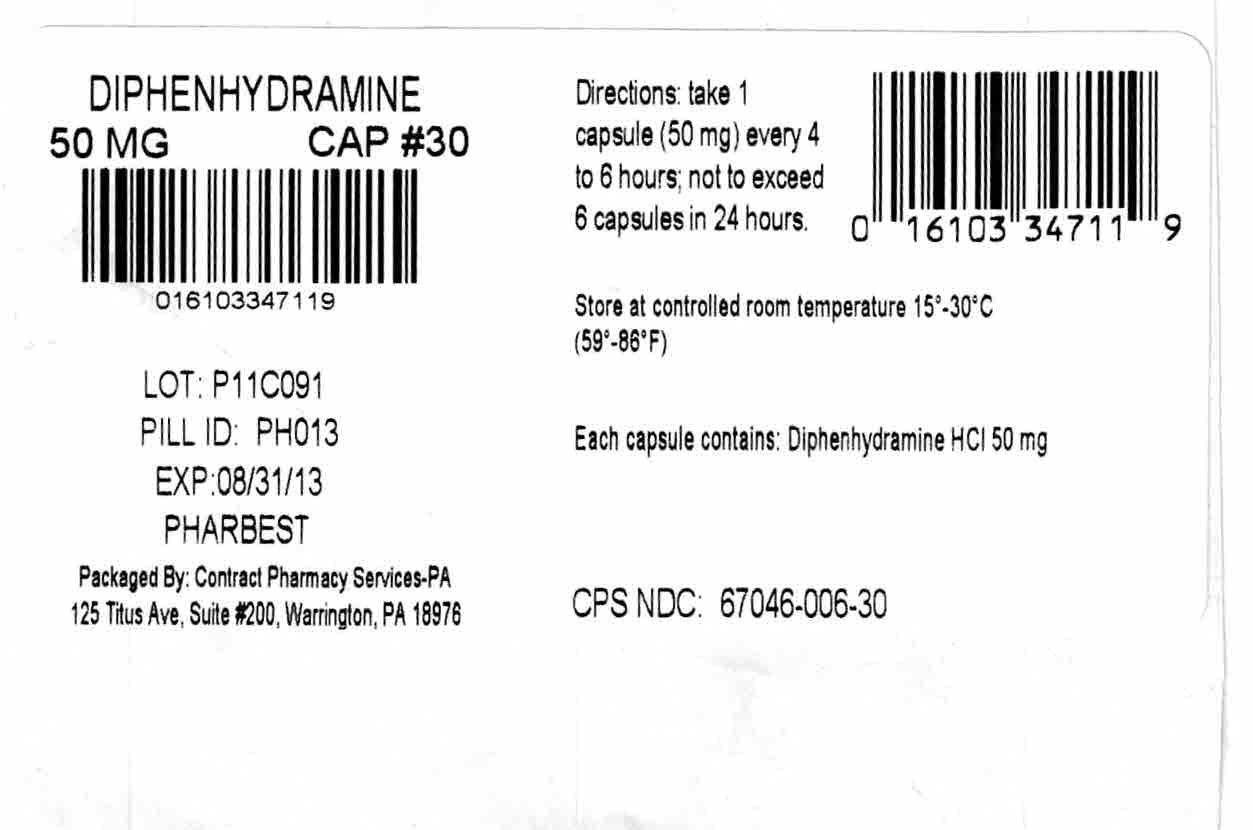 DRUG LABEL: Pharbedryl
NDC: 67046-006 | Form: CAPSULE
Manufacturer: Contract Pharmacy Services-PA
Category: otc | Type: HUMAN OTC DRUG LABEL
Date: 20170911

ACTIVE INGREDIENTS: DIPHENHYDRAMINE HYDROCHLORIDE 50 mg/1 1
INACTIVE INGREDIENTS: FERROSOFERRIC OXIDE; D&C RED NO. 28; FD&C BLUE NO. 1; FD&C RED NO. 40; GELATIN; LACTOSE MONOHYDRATE; MAGNESIUM STEARATE; SILICON DIOXIDE; SODIUM LAURYL SULFATE

Diphenhydramine 50 mg #30 006
Drug Facts

Active ingredient(in each banded capsule)

Diphenhydramine HCl 50 mg

Purpose

Antihistamine

Uses:

Temporarily relieves these symptoms associated with the common cold, hay fever, or other respiratory allergies:

- Sneezing
- Nasal congestion
- Runny nose
- Itchy, watery eyes

Do not use

- With any other product containing diphenhydramine, even one used on skin.

Ask a doctor before use if you have

- Trouble urinating due to enlarged prostate gland
- A breathing problem such as emphysema or chronic bronchitis
- Glaucoma

Ask doctor or pharmacist before use if you are

taking sedatives or tranquilizers

When using this product

- Avoid alcoholic drinks
- Marked drowsiness may occur.
- Excitability may occur, especially in children
- Alcohol, sedatives and tranquilizers may increase drowsiness
- Be careful when driving a motor vehicle or operating machinery

If pregnant or breast-feeding,

ask a health professional before use.

Keep out of reach of children.

In case of accidental overdose, get medical help or contact a Poison Control Center immediately.

Directions:

- Take every 4-6 hours
- Do not take more than 6 doses in 24 hours.

Adults and children 12 years or over | 1 capsule
Children under 12 years | ask a doctor

Other information:

- Tamper Evident: Do not use if safety seal under cap is broken or missing
- Store at room temperature 15°-30°C (59°-86°F)
- Protect from moisture
- Use by expiration date on package

Questions? Adverse drug event call:

(866) 562-2756